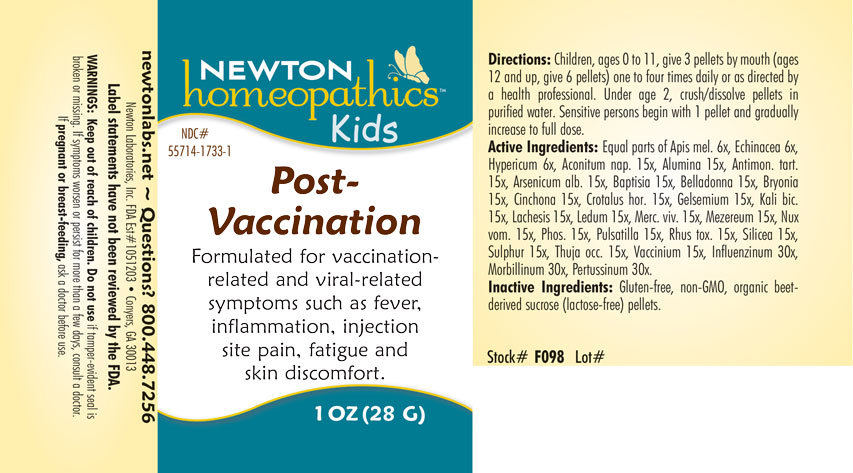 DRUG LABEL: Post-Vaccination
NDC: 55714-1733 | Form: PELLET
Manufacturer: Newton Laboratories, Inc.
Category: homeopathic | Type: HUMAN OTC DRUG LABEL
Date: 20201123

ACTIVE INGREDIENTS: INFLUENZA A VIRUS 30 [hp_X]/1 g; INFLUENZA B VIRUS 30 [hp_X]/1 g; MEASLES VIRUS 30 [hp_X]/1 g; HUMAN SPUTUM, BORDETELLA PERTUSSIS INFECTED 30 [hp_X]/1 g; ACONITUM NAPELLUS 15 [hp_X]/1 g; ALUMINUM OXIDE 15 [hp_X]/1 g; ANTIMONY POTASSIUM TARTRATE 15 [hp_X]/1 g; ARSENIC TRIOXIDE 15 [hp_X]/1 g; BAPTISIA TINCTORIA ROOT 15 [hp_X]/1 g; ATROPA BELLADONNA 15 [hp_X]/1 g; BRYONIA ALBA ROOT 15 [hp_X]/1 g; CINCHONA OFFICINALIS BARK 15 [hp_X]/1 g; CROTALUS HORRIDUS HORRIDUS VENOM 15 [hp_X]/1 g; GELSEMIUM SEMPERVIRENS ROOT 15 [hp_X]/1 g; POTASSIUM DICHROMATE 15 [hp_X]/1 g; LACHESIS MUTA VENOM 15 [hp_X]/1 g; LEDUM PALUSTRE TWIG 15 [hp_X]/1 g; MERCURY 15 [hp_X]/1 g; DAPHNE MEZEREUM BARK 15 [hp_X]/1 g; STRYCHNOS NUX-VOMICA SEED 15 [hp_X]/1 g; PHOSPHORUS 15 [hp_X]/1 g; PULSATILLA VULGARIS 15 [hp_X]/1 g; TOXICODENDRON PUBESCENS LEAF 15 [hp_X]/1 g; SILICON DIOXIDE 15 [hp_X]/1 g; SULFUR 15 [hp_X]/1 g; THUJA OCCIDENTALIS LEAFY TWIG 15 [hp_X]/1 g; BILBERRY 15 [hp_X]/1 g; APIS MELLIFERA 6 [hp_X]/1 g; ECHINACEA, UNSPECIFIED 6 [hp_X]/1 g; HYPERICUM PERFORATUM 6 [hp_X]/1 g
INACTIVE INGREDIENTS: SUCROSE

Post-Vac 1733P

OTC - KEEP OUT OF REACH OF CHILDREN SECTION

Keep out of reach of children.

OTC - PREGNANCY OR BREAST FEEDING SECTION

If pregnant or breast-feeding, ask a doctor before use.

WARNINGS SECTION

WARNINGS: Keep out of reach of children. Do not use if tamper-evident seal is broken or missing. If symptoms worsen or persist for more than a few days, consult a doctor. If pregnant or breast-feeding, ask a doctor before use.

QUESTIONS SECTION

newtonlabs.net - Questions? 1.800.448.7256

Newton Laboratories, Inc. FDA Est # 1051203 - Conyers, GA 30013

OTC - PURPOSE SECTION

Formulated for vaccination-related and viral-related symptoms such as fever, inflammation, injection site pain, fatigue and skin discomfort.

INACTIVE INGREDIENT SECTION

Inactive Ingredients: Gluten-free, non-GMO, organic beet-derived sucrose (lactose-free) pellets.

OTC - ACTIVE INGREDIENT SECTION

Equal parts of Apis mel. 6x, Echinacea 6x, Hypericum 6x, Aconitum nap. 15x, Alumina 15x, Antimon. tart.15x, Baptisia 15x, Bryonia 15x, Cinchona 15x, Crotalus horridus 15x, Gelsemium 15x, Kali bic. 15x, Lachesis 15x, Ledum 15x, Merc. viv. 15x, Mezereum 15x, Phosphorus 15x, Pulsatilla 15x, Rhus toxicodendron 15x, Silicea 15x, Sulphur 15x, Thuja occ. 15x, Vaccinium 15x, Arsenicum alb. 15x, Belladonna 15x, Nux vom. 15x, Influenzinum 30x, Morbillinum 30x, Pertussinum 30x.

DOSAGE & ADMINISTRATION SECTION

Directions: Children, ages 0 to 11, give 3 pellets by mouth (ages 12 and up, give 6 pellets) one to four times daily or as directed by a health professional. Under age 2, crush or dissolve pellets in purified water. Sensitive persons begin with 1 pellet and gradually increase to full dose.

INDICATIONS & USAGE SECTION

Formulated for vaccination-related and viral-related symptoms such as fever, inflammation, injection site pain, fatigue and skin discomfort.